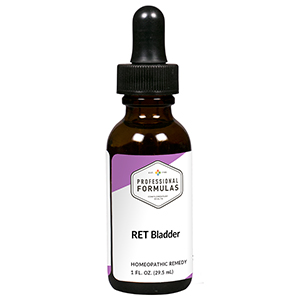 DRUG LABEL: RET Bladder
NDC: 63083-7006 | Form: LIQUID
Manufacturer: Professional Complementary Health Formulas
Category: homeopathic | Type: HUMAN OTC DRUG LABEL
Date: 20190815

ACTIVE INGREDIENTS: CENTAURIUM ERYTHRAEA FLOWERING TOP 3 [hp_X]/29.5 mL; CERATOSTIGMA WILLMOTTIANUM FLOWERING TOP 3 [hp_X]/29.5 mL; CARPINUS BETULUS FLOWER 3 [hp_X]/29.5 mL; SALIX ALBA FLOWERING TOP 3 [hp_X]/29.5 mL; POTASSIUM PHOSPHATE, UNSPECIFIED FORM 3 [hp_X]/29.5 mL; SODIUM CHLORIDE 3 [hp_X]/29.5 mL; POTASSIUM ALUM 30 [hp_X]/29.5 mL; APIS MELLIFERA 30 [hp_X]/29.5 mL; ACTIVATED CHARCOAL 30 [hp_X]/29.5 mL; ARTEMISIA CINA PRE-FLOWERING TOP 30 [hp_X]/29.5 mL; PULSATILLA MONTANA WHOLE 30 [hp_X]/29.5 mL; SEPIA OFFICINALIS JUICE 30 [hp_X]/29.5 mL; SPONGIA OFFICINALIS SKELETON, ROASTED 30 [hp_X]/29.5 mL; DELPHINIUM STAPHISAGRIA SEED 30 [hp_X]/29.5 mL; VERATRUM ALBUM ROOT 30 [hp_X]/29.5 mL
INACTIVE INGREDIENTS: ALCOHOL; WATER

RET6

ACTIVE INGREDIENTS

Centaury flower essence 3X
Cerato flower essence 3X
Hornbeam flower essence 3X
Willow flower essence 3X
Kali phosphoricum 3X, 6X, 30X
Natrum muriaticum 3X, 6X, 30X
and all the following at 30X, 100X, 200X:
Alumen
Apis mellifica
Carbo vegetabilis
Cina
Pulsatilla
Sepia
Spongia tosta
Staphysagria
Veratrum album

QUESTIONS

Professional Formulas

PO Box 2034 Lake Oswego, OR 97035

INDICATIONS

Temporarily relieves passiveness or being weak-willed, lacking confidence or trust in ones self, mental weariness, staleness in life, self-pity, bitterness, grief, despair, or sadness.*

PURPOSE

*Claims based on traditional homeopathic practice, not accepted medical evidence. Not FDA evaluated.

WARNINGS

In case of overdose, get medical help or contact a poison control center right away.

Keep out of the reach of children.

PREGNANCY OR BREAST FEEDING

If pregnant or breastfeeding, ask a healthcare professional before use.

DIRECTIONS

Place drops under tongue 30 minutes before/after meals. Adults and children 12 years and over: Take 5 drops up to 4 times per day for up to one month. Consult a physician for use in children under 12 years of age.

OTHER INFORMATION

Tamper resistant. If seal is broken, do not use. After opening, close container tightly and store at room temperature away from heat.

INACTIVE INGREDIENTS

20% ethanol, purified water.

LABEL

Est 1985

Professional Formulas

Complementary Health

RET Bladder

Homeopathic Remedy

1 FL. OZ. (29.5 mL)